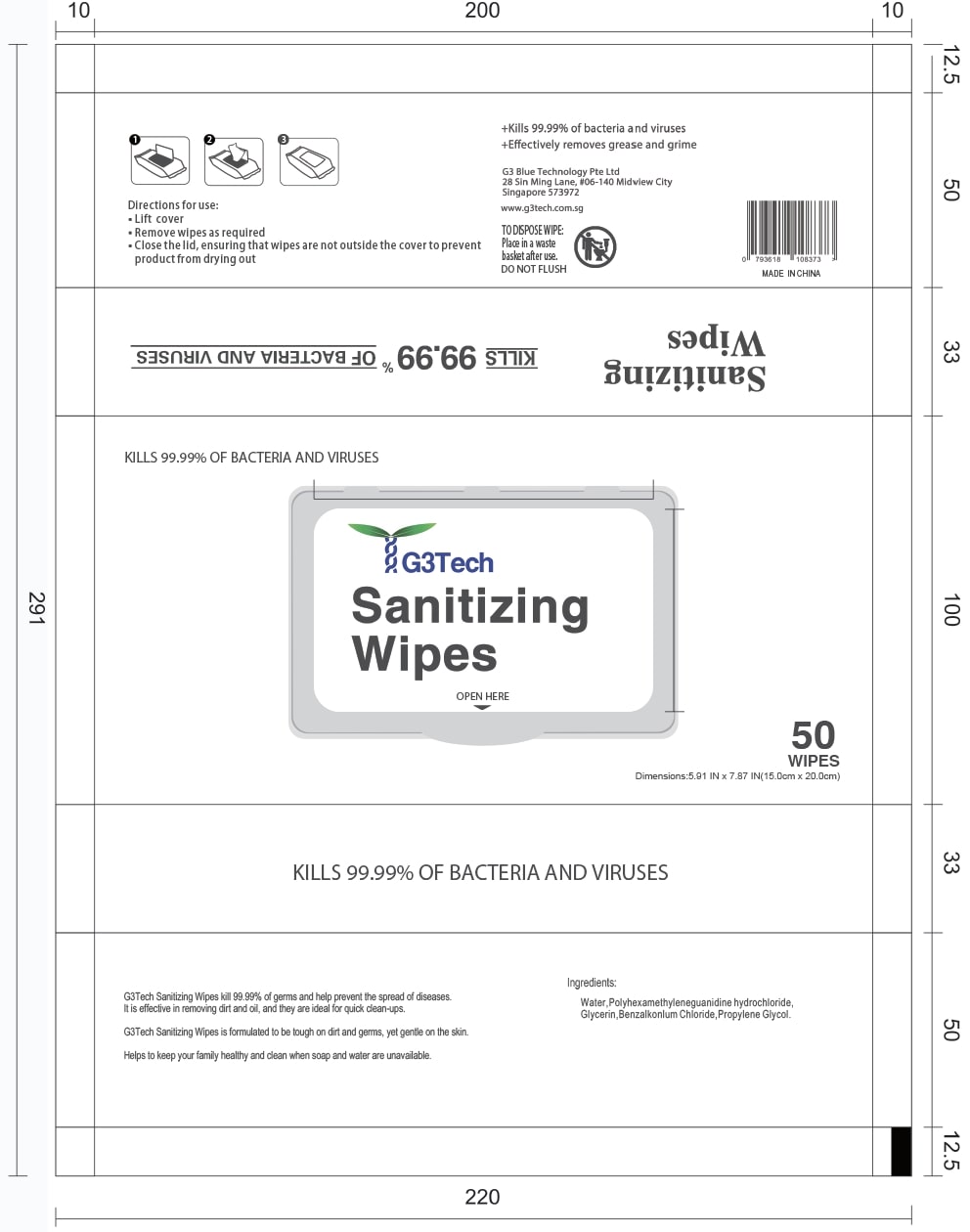 DRUG LABEL: G3Tech Sanitizing Wipes
NDC: 80062-002 | Form: CLOTH
Manufacturer: G3 Blue Technology Pte Ltd
Category: otc | Type: HUMAN OTC DRUG LABEL
Date: 20200813

ACTIVE INGREDIENTS: BENZALKONIUM CHLORIDE 0.13 1/1 1
INACTIVE INGREDIENTS: DECYL GLUCOSIDE; ALOE VERA LEAF; ETHYLHEXYLGLYCERIN; PHENOXYETHANOL; GLYCERIN; WATER

Active Ingredient(s)

Benzalkonium Chloride 0.13% v/v. Purpose: Antiseptic

Purpose

Antiseptic, Cloth

Use

Sanitizing wipes to help kill 99.99% of germs and help prevent the spread of diseases. Effective in removing dirt and oil, and ideal for quick clean-ups. For use when soap and water are not available.

Warnings

For External Use Only.

Directions

- Lift cover
- Remove wipes as required
- Close the lid, ensuring that wipes are not outside the cover to prevent product from drying out

Other information

- Store in a cool dry place
- Keep away from direct sunlight

Inactive ingredients

Aqua

Glycerin

Ethylhexylglycerin

Phenoxyethanol

Propylene Glycol

Decyl Glucoside

Aloe Barbadensis Leaf Extract

Keep out of reach of children.

Package Label - Principal Display Panel

50pcs NDC: 80062-002-01